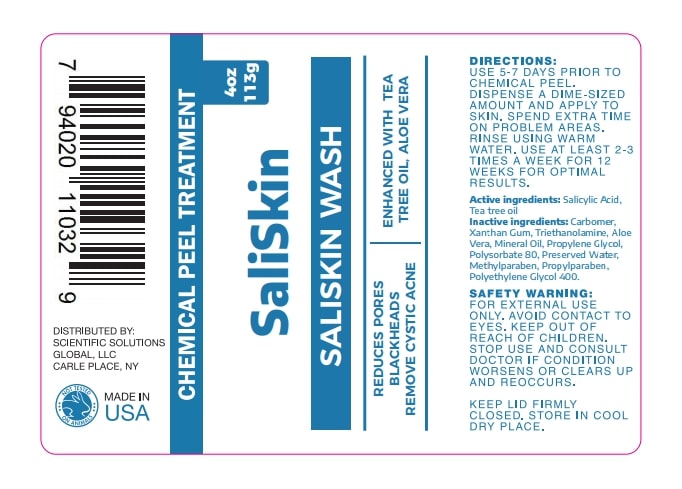 DRUG LABEL: SaliSkin Wash
NDC: 71718-501 | Form: GEL
Manufacturer: Scientific Solutions Global LLC
Category: otc | Type: HUMAN OTC DRUG LABEL
Date: 20191004

ACTIVE INGREDIENTS: SALICYLIC ACID 2 g/2 g
INACTIVE INGREDIENTS: CARBOMER 980; XANTHAN GUM; ALOE VERA LEAF POLYSACCHARIDES; MINERAL OIL; PROPYLENE GLYCOL; POLYSORBATE 80; WATER; METHYLPARABEN; PROPYLPARABEN; TEA TREE OIL; TROLAMINE; POLYETHYLENE GLYCOL 400

PACKAGE LABEL

ACTIVE INGREDIENT

SALICYLIC ACID, TEA TREE OIL

INACTIVE INGREDIENT

CARBOMER, XANTHAM GUM, TRIETHANOLAMINE, ALOE VERA, MINERAL OIL, PROPYLENE GLYCOL, POLYSORBATE 80, PRESERVED WATER, METHYLPARABEN, PROPYLPARABEN, POLYETHYLENE GLYCOL 400

DOSAGE AND ADMINISTRATION

USE 5-6 PRIOR TO CHEMICAL PEEL.

DISPENSE A DIME-SIZED AMOUNT AND APPLY TO SKIN.

SPEND EXTRA TIME ON PROBLEM AREAS

RINSE USING WARM WATER.

USE AT LEAST 2-3 TIMES A WEEK FOR 12 WEEKS FOR OPTIMAL RESULTS

WARNINGS

FOR EXTERNAL USE ONLY.

AVOID CONTACT TO EYES.

KEEP OUT OF REACH OF CHILDREN.

STOP USE AND CONSULT DOCTOR IF CONDITION WORSENS OR CLEARS UP AND REOCCURS

PURPOSE

REDUCES PORES

BLACKHEADS

REMOVE CYSTIC ACNE

KEEP OUT OF REACH OF CHILDREN

INDICATIONS AND USAGE

REDUCES PORES

BLACKHEADS

REMOVE CYSTIC ACNE